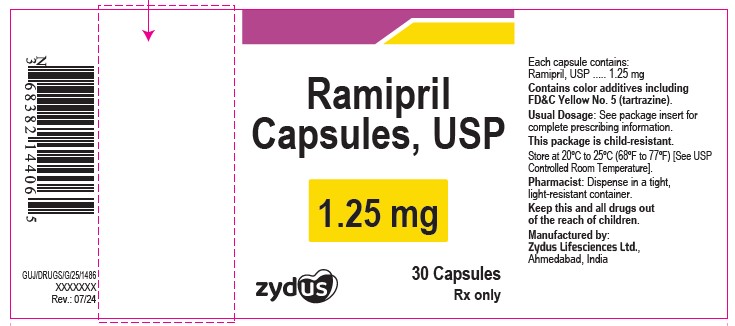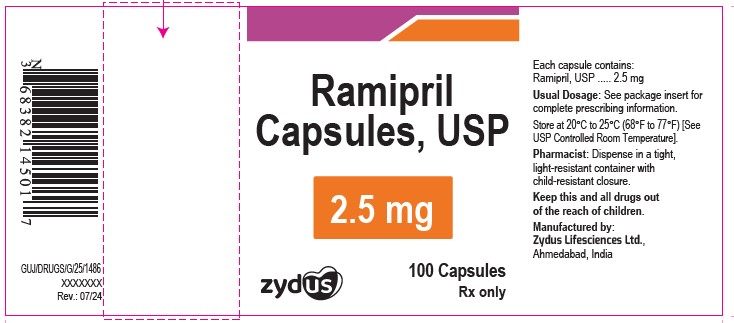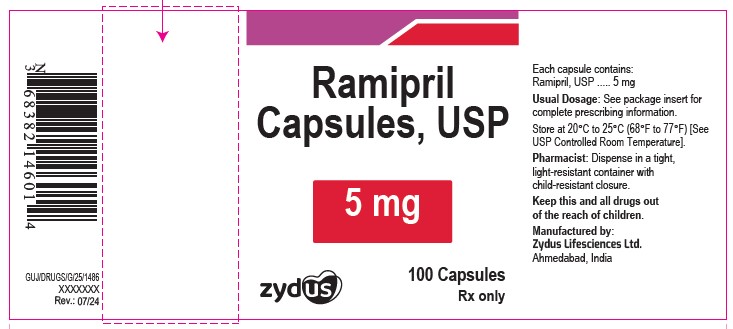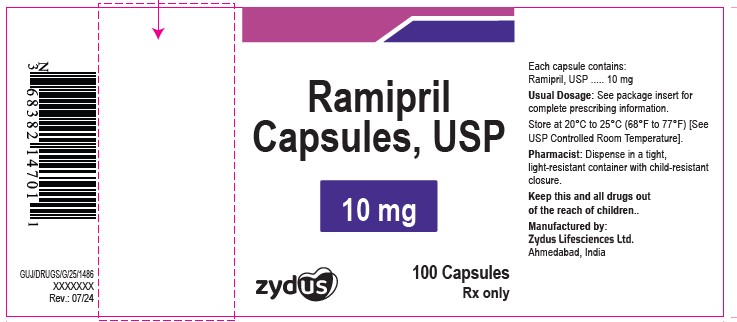 DRUG LABEL: Ramipril
NDC: 65841-655 | Form: CAPSULE
Manufacturer: Zydus Lifesciences Limited
Category: prescription | Type: HUMAN PRESCRIPTION DRUG LABEL
Date: 20241204

ACTIVE INGREDIENTS: RAMIPRIL 1.25 mg/1 1
INACTIVE INGREDIENTS: FD&C RED NO. 40; FD&C YELLOW NO. 5; FD&C YELLOW NO. 6; GELATIN; TITANIUM DIOXIDE; STARCH, CORN; FERROSOFERRIC OXIDE

RAMIPRIL CAPSULES

PACKAGE LABEL.PRINCIPAL DISPLAY PANEL

NDC 65841-655-06 in bottle of 30 Capsules

Ramipril Capsules, 1.25 mg

Rx only

30 Capsules

NDC 65841-656-01 in bottle of 100 Capsules

Ramipril Capsules, 2.5 mg

Rx only

100 Capsules

NDC 65841-657-01 in bottle of 100 Capsules

Ramipril Capsules, 5 mg

Rx only

100 Capsules

NDC 65841-658-01 in bottle of 100 Capsules

Ramipril Capsules, 10 mg

Rx only

100 Capsules